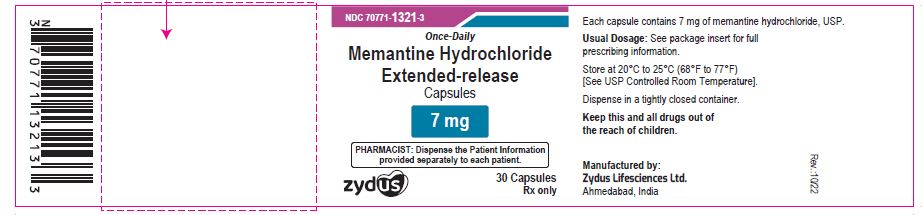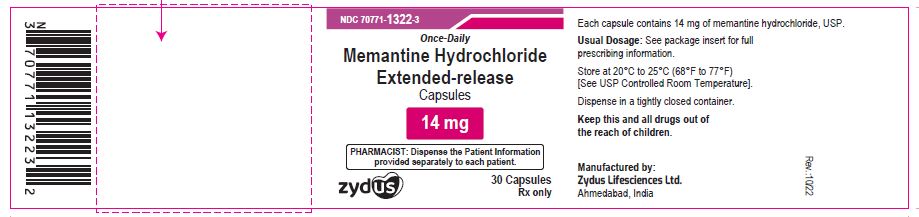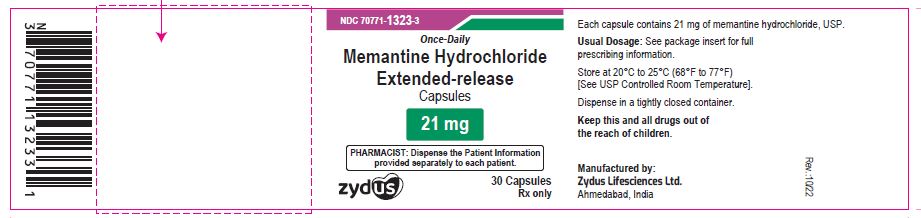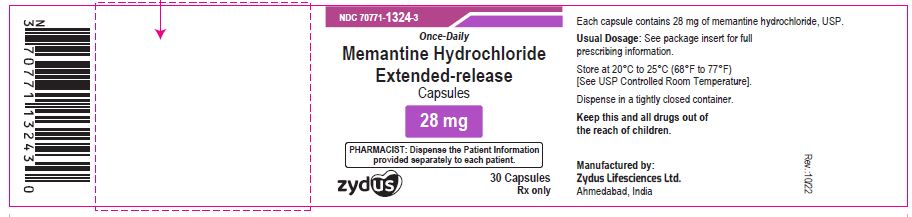 DRUG LABEL: Memantine hydrochloride
NDC: 70771-1321 | Form: CAPSULE, EXTENDED RELEASE
Manufacturer: Zydus Lifesciences Limited
Category: prescription | Type: HUMAN PRESCRIPTION DRUG LABEL
Date: 20241130

ACTIVE INGREDIENTS: MEMANTINE HYDROCHLORIDE 7 mg/1 1
INACTIVE INGREDIENTS: AMMONIA; ALCOHOL; BUTYL ALCOHOL; ETHYLCELLULOSE (7 MPA.S); GELATIN; HYPROMELLOSES; FERROSOFERRIC OXIDE; ISOPROPYL ALCOHOL; POTASSIUM HYDROXIDE; PROPYLENE GLYCOL; SHELLAC; SODIUM LAURYL SULFATE; SUCROSE; TALC; TRIETHYL CITRATE; TITANIUM DIOXIDE; WATER

MEMANTINE HYDROCHLORIDE EXTENDED-RELEASE CAPSULES

PACKAGE LABEL.PRINCIPAL DISPLAY PANEL

Memantine Hydrochloride Extended-release Capsules, 7 mg

NDC 70771-1321-3

30 Counts

Memantine Hydrochloride Extended-release Capsules, 14 mg

70771-1322-3

30 Counts

Memantine Hydrochloride Extended-release Capsules, 21 mg

NDC 70771-1323-3

30 Counts

Memantine Hydrochloride Extended-release Capsules, 28 mg

NDC 70771-1324-3

30 Counts